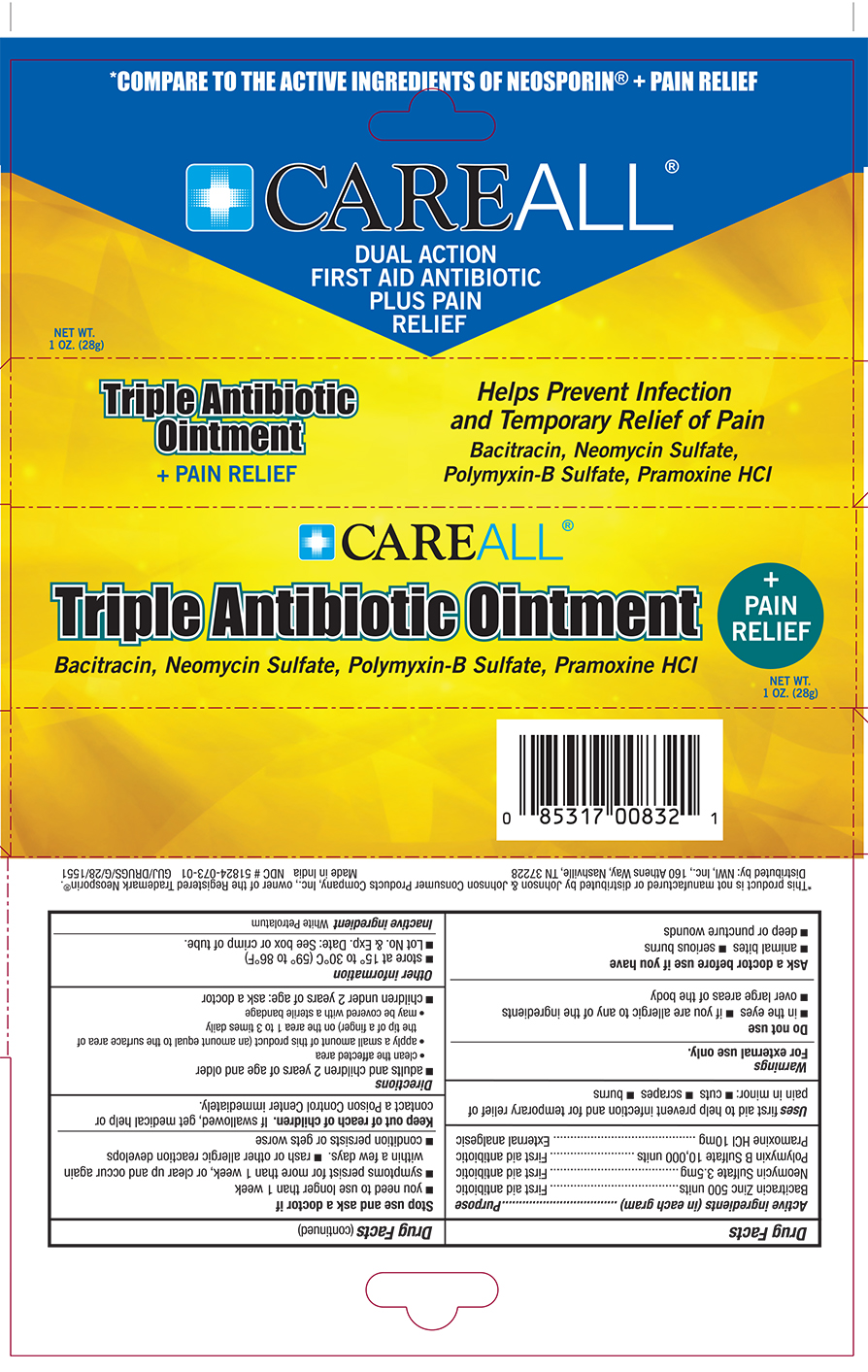 DRUG LABEL: CareALL Triple Antibiotic plus Pain Relief
NDC: 51824-073 | Form: OINTMENT
Manufacturer: New World Imports, Inc
Category: otc | Type: HUMAN OTC DRUG LABEL
Date: 20190823

ACTIVE INGREDIENTS: BACITRACIN ZINC 500 [USP'U]/1 g; NEOMYCIN SULFATE 3.5 mg/1 g; POLYMYXIN B SULFATE 10000 [USP'U]/1 g; PRAMOXINE HYDROCHLORIDE 10 mg/1 g
INACTIVE INGREDIENTS: PETROLATUM

Active Ingredients (in each gram)

Bacitracin Zinc 500 units

Neomycin Sulfate 3.5 mg

Polymyxin B Sulfate 10,000 units

Pramoxine HCl 10mg

PURPOSE

First aid antibiotic (Bacitracin Zinc 500 units, Neomycin Sulfate 3.5 mg, & Polymyxin B Sulfate 10,000 units)

External Analgesic (Pramoxine HCl 10mg)

KEEP OUT OF REACH OF CHILDREN

If swallowed, get medical help or contact a poison control center immediately

INDICATIONS AND USAGE

First aid to help prevent infection and for temporary relief of pain in minor cuts, scrapes and burns

WARNINGS

For external use only

Do not use

In the eyes

If you are allergic to any of the ingredients

Over large areas of the body

Ask a doctor before use if you have

Animal bites

Serious Burns

Deep or puncture wounds

Stop use and ask a doctor if

You need to use longer than 1 week

condition persists or gets worse

rash or other allergic reaction develops

symptoms persist for more than 1 week, or clear up and occur again within a few days

DOSAGE AND ADMINISTRATION

Adults and childre 2 years of age and older:

- Clean the affected area
- Apply a small amount of this product (an amount equal to the surface of th tip of a finger) on the area 1 to 3 times daily
- May be covered with a sterile bandage

Children under 2 years of age: ask a doctor

INACTIVE INGREDIENT

White Petrolatum